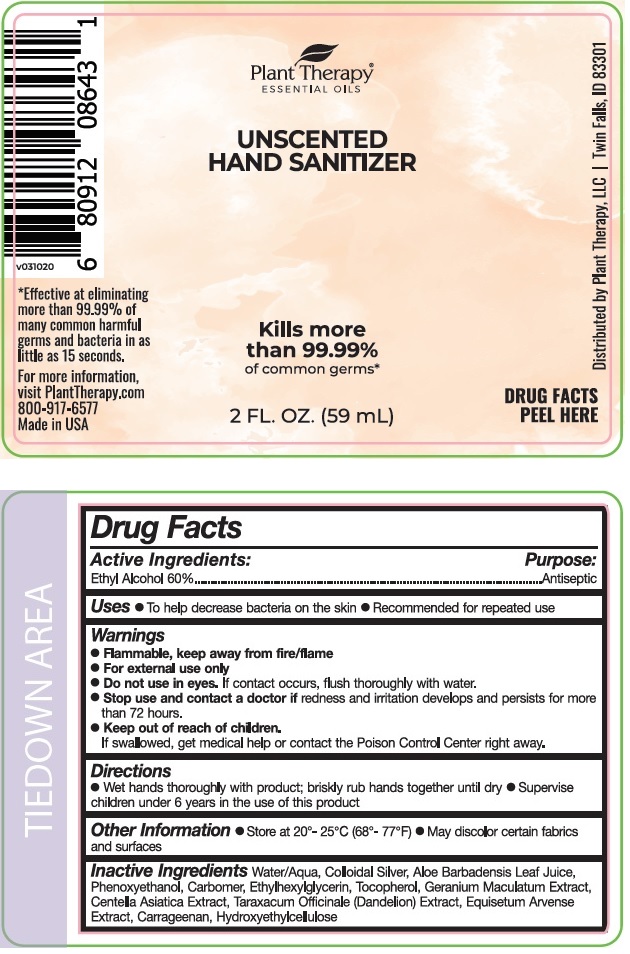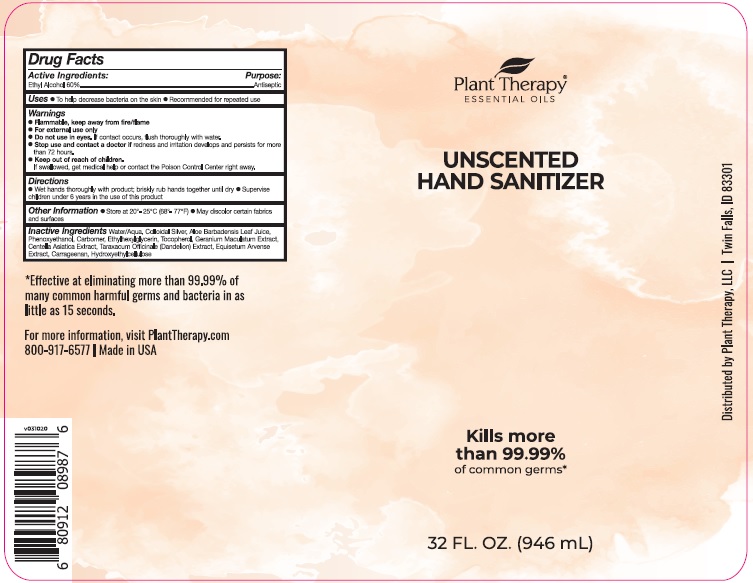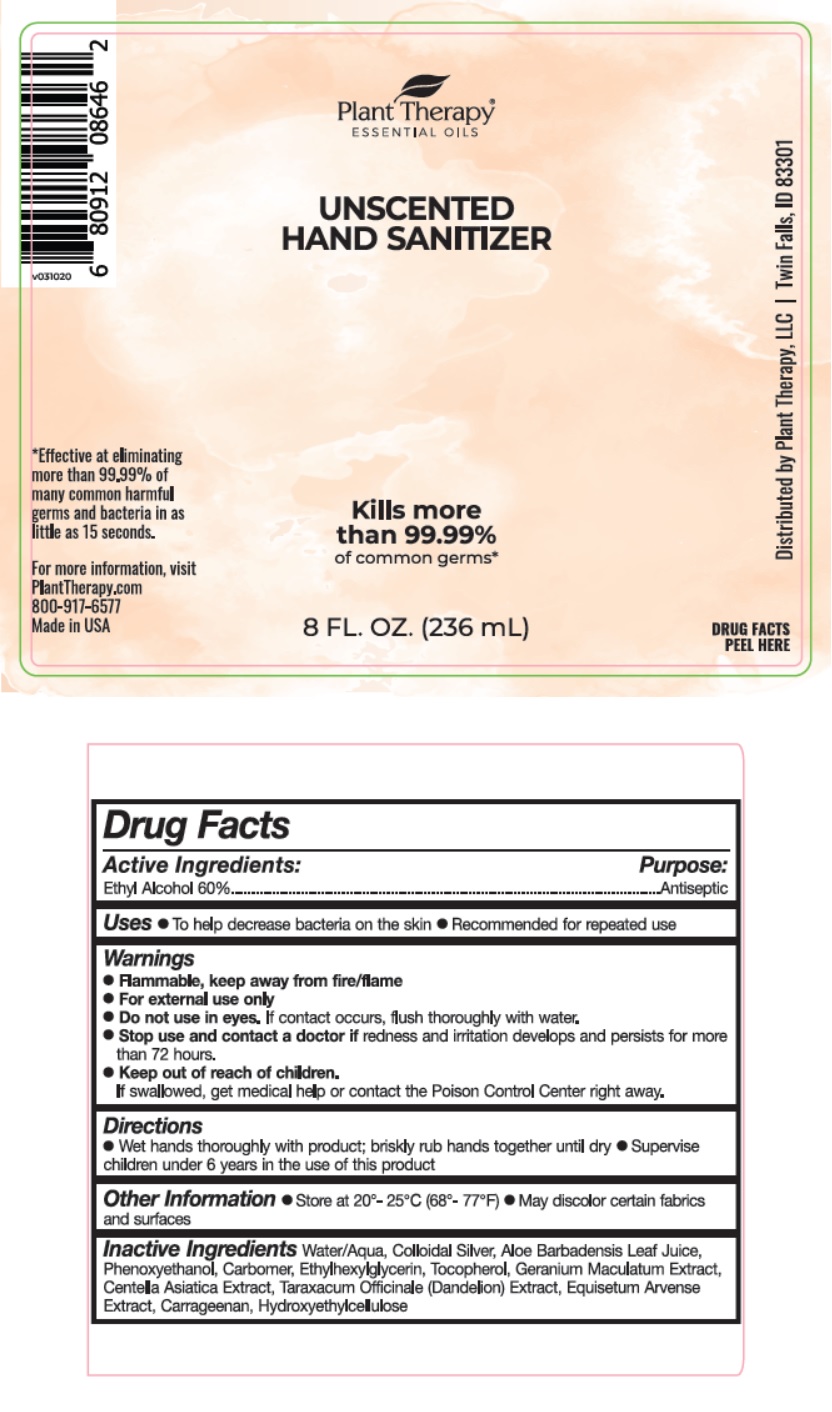 DRUG LABEL: Unscented Hand Sanitizer Gel
NDC: 74877-120 | Form: GEL
Manufacturer: Plant Therapy, LLC
Category: otc | Type: HUMAN OTC DRUG LABEL
Date: 20200727

ACTIVE INGREDIENTS: ALCOHOL 60 mL/100 mL
INACTIVE INGREDIENTS: WATER; SILVER; ALOE VERA LEAF; PHENOXYETHANOL; CARBOMER HOMOPOLYMER, UNSPECIFIED TYPE; ETHYLHEXYLGLYCERIN; TOCOPHEROL; GERANIUM MACULATUM ROOT; CENTELLA ASIATICA WHOLE; TARAXACUM OFFICINALE; EQUISETUM ARVENSE BRANCH; CARRAGEENAN; HYDROXYETHYL CELLULOSE, UNSPECIFIED

Plant Therapy® ESSENTIAL OILS UNSCENTED HAND SANITIZER

Active Ingredients:

Ethyl Alcohol 60%

Purpose:

Antiseptic

INDICATIONS AND USAGE

Uses • To help decrease bacteria on the skin • Recommended for repeated use

Warnings

- Flammable, keep away from fire/flame
- For external use only
- Do not use in eyes. If contact occurs, flush thoroughly with water.
- Stop use and contact a doctor if redness and irritation develops and persists for more than 72 hours.

• Keep out of reach of children.

If swallowed, get medical help or contact a Poison Control Center right away.

Directions

• Wet hands thoroughly with product; briskly rub hands together until dry • Supervise children under 6 years in the use of this product

Other Information • Store at 20°-25°C (68°-77°F) • May discolor certain fabrics and surfaces

INACTIVE INGREDIENT

Inactive Ingredients Water/Aqua, Colloidal Silver, Aloe Barbadensis Leaf Juice, Phenoxyethanol, Carbomer, Ethylhexylglycerin, Tocopherol, Geranium Maculatum Extract, Centella Asiatica Extract, Taraxacum Officinale (Dandelion) Extract, Equisetum Arvense Extract, Carrageenan, Hydroxyethylcellulose

Kills more than 99.99% of common germs*

*Effective at eliminating more than 99.99% of many common harmful germs and bacteria in as little as 15 seconds.

For more information, visit PlantTherapy.com 800-917-6577

Made in USA

Distributed by Plant Therapy, LLC | Twin Falls, ID 83301